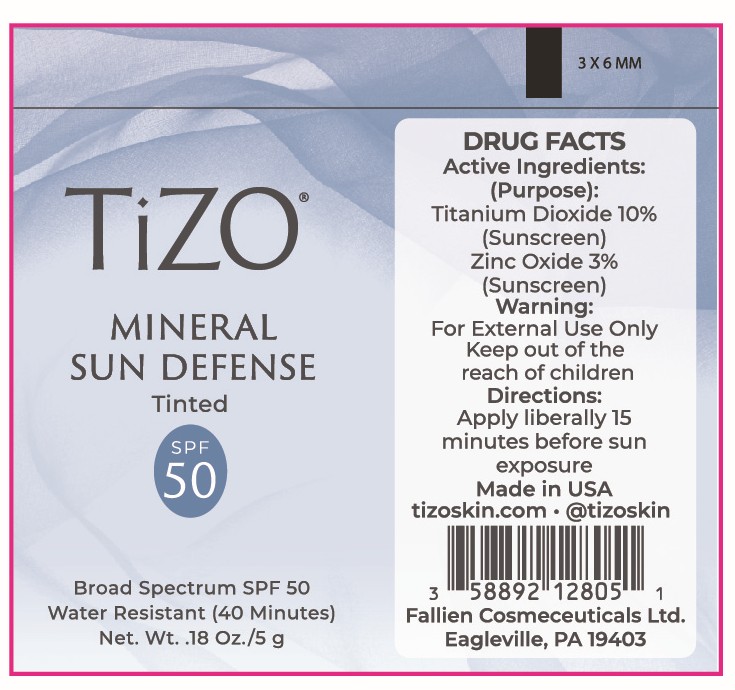 DRUG LABEL: TiZO Mineral Sun Defense SPF 50
NDC: 58892-128 | Form: CREAM
Manufacturer: Fallien Cosmeceuticals Ltd.
Category: otc | Type: HUMAN OTC DRUG LABEL
Date: 20250131

ACTIVE INGREDIENTS: TITANIUM DIOXIDE 100 mg/1 g; ZINC OXIDE 30 mg/1 g
INACTIVE INGREDIENTS: GLYCERIN; MELISSA OFFICINALIS WHOLE; MICA; MICROCRYSTALLINE WAX; PEG-30 DIPOLYHYDROXYSTEARATE; TRIETHOXYCAPRYLYLSILANE; CAPRYLIC/CAPRIC TRIGLYCERIDE; CYCLOHEXASILOXANE; CYCLOPENTASILOXANE; BISMUTH OXYCHLORIDE; CAPRYLHYDROXAMIC ACID; OCTYLDODECYL NEOPENTANOATE; CETEARETH-20; IRON OXIDES; TETRAHEXYLDECYL ASCORBATE; ALPHA-TOCOPHEROL ACETATE; ISOHEXADECANE; WATER; CAPRYLYL GLYCOL; ISODODECANE; SODIUM CHLORIDE; TOCOPHEROL; TRIETHANOLAMINE; ETHYLHEXYL HYDROXYSTEARATE BENZOATE; DIMETHICONE; EDETATE DISODIUM ANHYDROUS

Active Ingredients:

Titanium Dioxide 10%, Zinc Oxide 3%

Purpose:

Sunscreen

Directions:

Apply liberally 15 minutes before sun exposure.

Warning:

For external use only.

Warning and Directions:

For external use only. Apply liberally 15 minutes before sun exposure.

INACTIVE INGREDIENT

Bismuth Oxychloride, Capric/Caprylic Triglyceride, Caprylhydroxamic Acid, Caprylyl Glycol, Ceteareth-20, Cyclohexasiloxane, Cyclopentasiloxane, Dimethicone, Disodium EDTA, Ethylhexyl Hydroxystearate Benzoate, Glycerin, Iron Oxides, Isododecane, Isohexadecane, Melissa Officinalis (Balm Mint) Extract, Mica, Microcrystalline Wax, Octyldodecyl Neopentanoate, PEG-30 Dipolyhydroxystearate, Sodium Chloride, Tetrahexyldecyl Ascorbate, Tocopheryl Acetate, Tocopherol, Triethanolamine, Triethoxycaprylylsilane, Water

Warning:

Keep out of the reach of children.